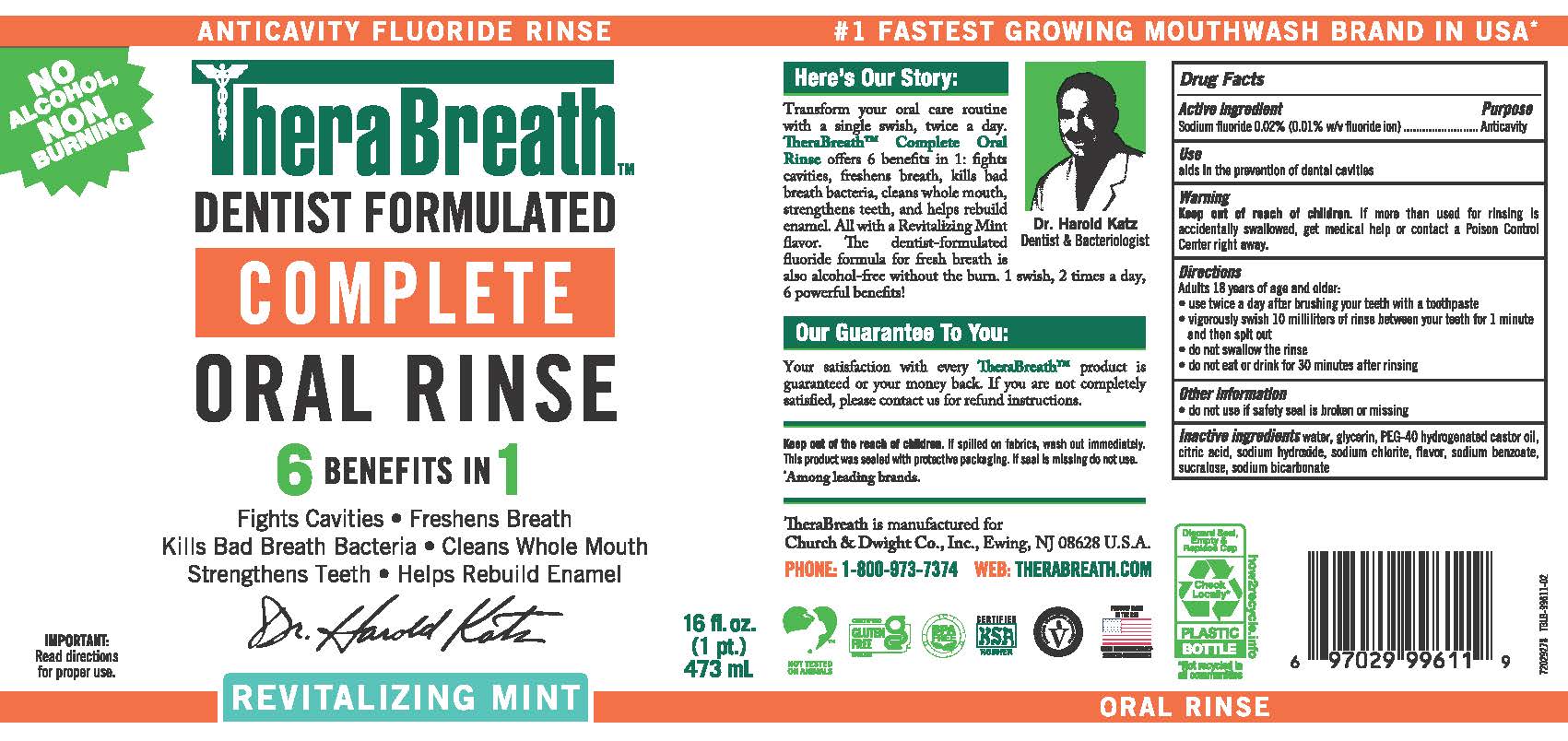 DRUG LABEL: TheraBreath Complete Oral Rinse
NDC: 10237-267 | Form: RINSE
Manufacturer: Church & Dwight Co., Inc.
Category: otc | Type: HUMAN OTC DRUG LABEL
Date: 20260223

ACTIVE INGREDIENTS: SODIUM FLUORIDE 0.002 mg/10 mL
INACTIVE INGREDIENTS: SUCRALOSE; PEG-40 HYDROGENATED CASTOR OIL; SODIUM BICARBONATE; CITRIC ACID; SODIUM HYDROXIDE; GLYCERIN; WATER; SODIUM CHLORITE; SODIUM BENZOATE

TheraBreath Complete Oral Rinse

ACTIVE INGREDIENT

Sodium fluoride 0.02% (0.01% w/v fluoride ion)

PURPOSE

Anticavity

USE

aids in the prevention of dental cavities

WARNING

Keep out of reach of children. If more than used for rinsing is accidentally swallowed, get medical help or contact a Poison Control Center right away.

DIRECTIONS

Adults 18 years of age and older:
• use twice a day after brushing your teeth with a toothpaste
• vigorously swish 10 milliliters of rinse between your teeth for 1 minute and then spit out
• do not swallow the rinse
• do not eat or drink for 30 minutes after rinsing

OTHER INFORMATION

• do not use if safety seal is broken or missing

INACTIVE INGREDIENTS

water, glycerin, PEG-40 hydrogenated castor oil, citric acid, sodium hydroxide, sodium chlorite, flavor, sodium benzoate, sucralose, sodium bicarbonate

PACKAGE LABEL

NO ALCOHOL,

NON BURNING

ANTICAVITY FLUORIDE RINSE

THERABREATHTM

DENTIST FORMULATED

COMPLETE

ORAL RINSE

6 BENEFITS IN 1

Fights Cavities • Freshens Breath

Kills Bad Breath Bacteria • Cleans Whole Mouth

Strengthens Teeth • Helps Rebuild Enamel

Dr. Harold Katz

REVITALIZING MINT

IMPORTANT: Read directions for proper use.

16 fl. oz. (1 pt.) 473 mL